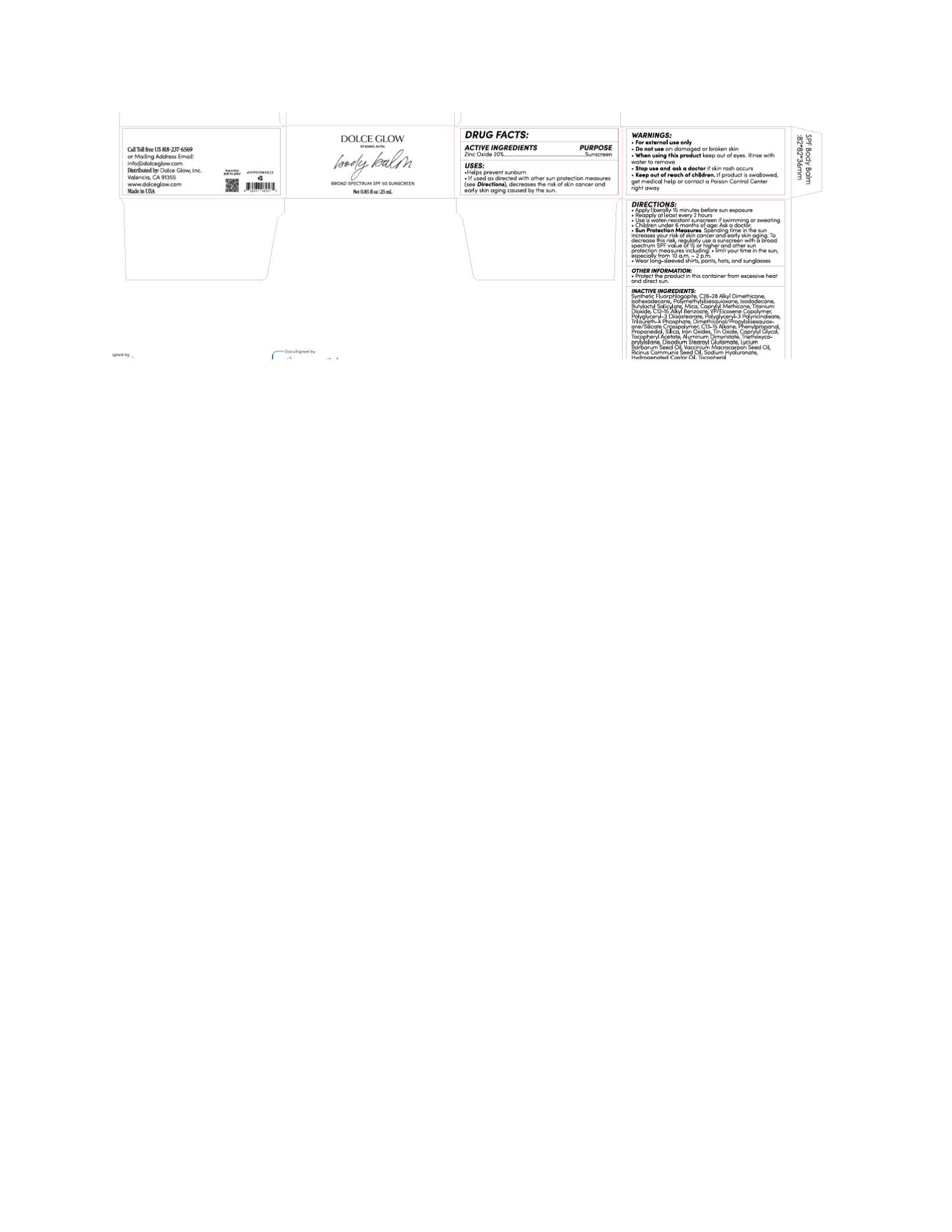 DRUG LABEL: Dolce Glow Body Balm
NDC: 83869-2167 | Form: LOTION
Manufacturer: Dolce Glow, Inc.
Category: otc | Type: HUMAN OTC DRUG LABEL
Date: 20251117

ACTIVE INGREDIENTS: ZINC OXIDE 220 mg/1 mL
INACTIVE INGREDIENTS: TRILAURETH-4 PHOSPHATE; VACCINIUM MACROCARPON (CRANBERRY) SEED OIL; SILICON DIOXIDE; TOCOPHEROL; CAPRYLYL GLYCOL; POLYGLYCERYL-3 DIISOSTEARATE; ALKYL (C12-15) BENZOATE; PROPANEDIOL; ISOHEXADECANE; CAPRYLYL METHICONE; TIN OXIDE; DIMETHICONOL/PROPYLSILSESQUIOXANE/SILICATE CROSSPOLYMER (450000000 MW); FERROSOFERRIC OXIDE; BUTYLOCTYL SALICYLATE; RICINUS COMMUNIS (CASTOR) SEED OIL; MICA; PHENYLPROPANOL; HYDROGENATED CASTOR OIL; ISODODECANE; TRIETHOXYCAPRYLYLSILANE; DISODIUM STEAROYL GLUTAMATE; SODIUM HYALURONATE; FERRIC OXIDE YELLOW; LYCIUM BARBARUM SEED OIL; TITANIUM DIOXIDE; POLYMETHYLSILSESQUIOXANE (4.5 MICRONS); ALUMINUM DIMYRISTATE; C13-15 ALKANE; FERRIC OXIDE RED

Dolce Glow Body Balm